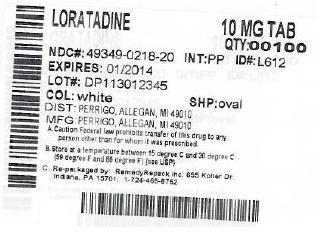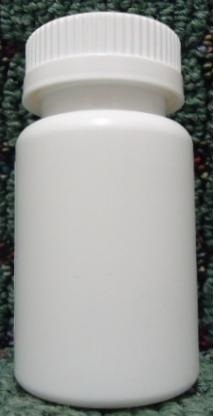 DRUG LABEL: Loratadineantihistamine
NDC: 49349-218 | Form: TABLET
Manufacturer: REMEDYREPACK INC. 
Category: prescription | Type: HUMAN PRESCRIPTION DRUG LABEL
Date: 20130520

ACTIVE INGREDIENTS: LORATADINE 10 mg/1 1
INACTIVE INGREDIENTS: LACTOSE MONOHYDRATE; POVIDONE; MAGNESIUM STEARATE; STARCH, CORN

Perrigo Loratadine Tablets, 10 mg Drug Facts

OTC - ACTIVE INGREDIENT

Loratadine 10 mg

OTC - PURPOSE

Antihistamine

INDICATIONS & USAGE

temporarily relieves these symptoms due to hay fever or other upper respiratory allergies:

- runny nose
- sneezing
- itchy, watery eyes
- itching of the nose or throat

WARNINGS

if you have ever had an allergic reaction to this product or any of its ingredients

liver or kidney disease. Your doctor should determine if you need a different dose.

do not take more than directed. Taking more than directed may cause drowsiness.

an allergic reaction to this product occurs. Seek medical help right away.

ask a health professional before use.

In case of overdose, get medical help or contact a Poison Control Center right away.

DOSAGE & ADMINISTRATION

adults and children 6 years and over | 1 tablet daily; not more than 1 tablet in 24 hours
children under 6 years of age | ask a doctor
consumers with liver or kidney disease | ask a doctor

STORAGE AND HANDLING

- do not use if printed foil under cap is broken or missing
- store at 20°-25°C (68°-77°F)

INACTIVE INGREDIENT

lactose monohydrate, magnesium stearate, povidone, pregelatinized starch

OTC - QUESTIONS

1-800-719-9260

PACKAGE LABEL.PRINCIPAL DISPLAY PANEL SECTION

DRUG: Loratadineantihistamine antihistamine

GENERIC: Loratadine

DOSAGE: TABLET

ADMINSTRATION: ORAL

NDC: 49349-218-20

ACTIVE INGREDIENT(S):

- LORATADINE 10mg in 1

INACTIVE INGREDIENT(S):

- LACTOSE MONOHYDRATE
- POVIDONE
- MAGNESIUM STEARATE
- STARCH, CORN

COLOR: white

SHAPE: OVAL

SCORE: No score

SIZE: 8 mm

IMPRINT: L612

PACKAGING: 100 in 1 VIAL